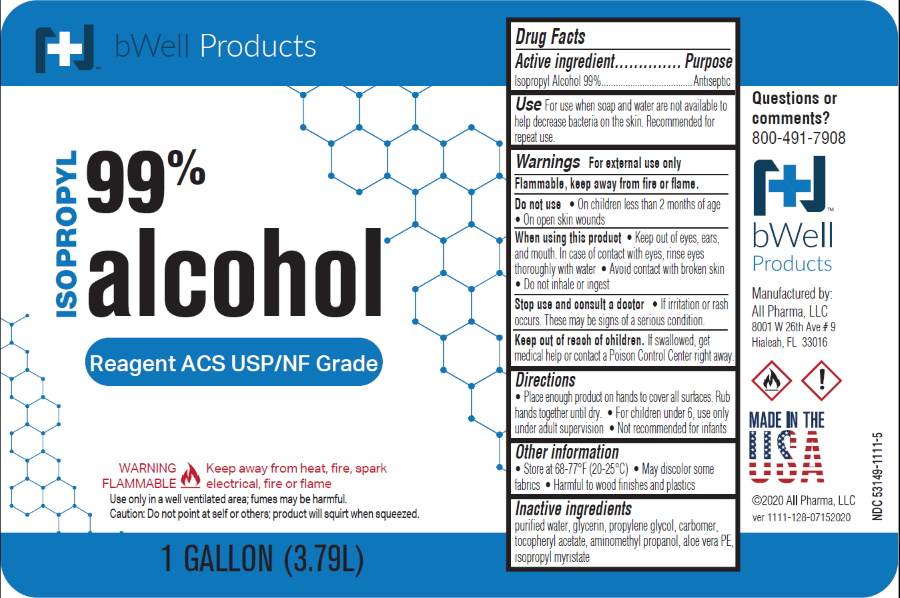 DRUG LABEL: Isopropyl Alcohol 99 Percent
NDC: 53149-1111 | Form: LIQUID
Manufacturer: All Pharma LLC
Category: otc | Type: HUMAN OTC DRUG LABEL
Date: 20200101

ACTIVE INGREDIENTS: ISOPROPYL ALCOHOL 990 mg/100 mL
INACTIVE INGREDIENTS: WATER

Isopropyl Alcohol 99 Percent

Active Ingredient

Isopropyl Alcohol 99% by volume

Purpose

First aid antiseptic

Use

First aid to help prevent the risk of infection in.

- minor cuts
- scrapes
- burns

Warnings

For external use only.

- Flammable, keep way from spark, heat and flame.

Ask a doctor before use for

- deep wounds
- animal bites
- serious burns

When using this product

• Do not inhale

• Do not apply over large areas of the body

• Do not use longer than 1 week

Stop use and ask a doctor if

condition persists or gets worse

Keep out of reach of children.

In case of accidental ingestion, seek professional assistance or contact a Poison Control Center immediately.

Directions

- clean the affected area.
- apply a small amount of this product on the affected area 1 to 3 times daily.
- may be covered with sterile bandage.
- if bandaged, let it dry first.

Inactive Ingredient

purified water

Principal Display Panel

ISOPROPYL
RUBBING
ALCOHOL 99%
USP
First Aid Antiseptic
NDC 53149-1111-1 Bottle of 16 fl oz (1 pt) 473 mL
NDC 53149-1111-3 Bottle of 32 fl oz (1 qt) 946 mL
NDC 53149-1111-5 Bottle of 128 fl oz (1 Gallon) 3.79 L